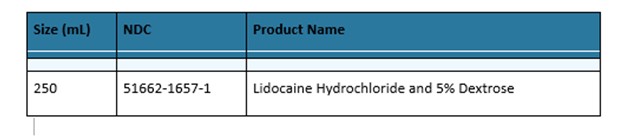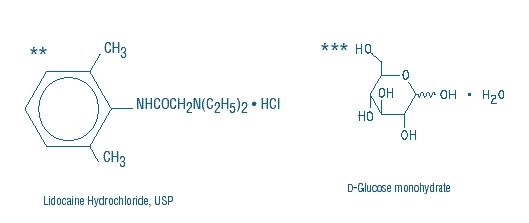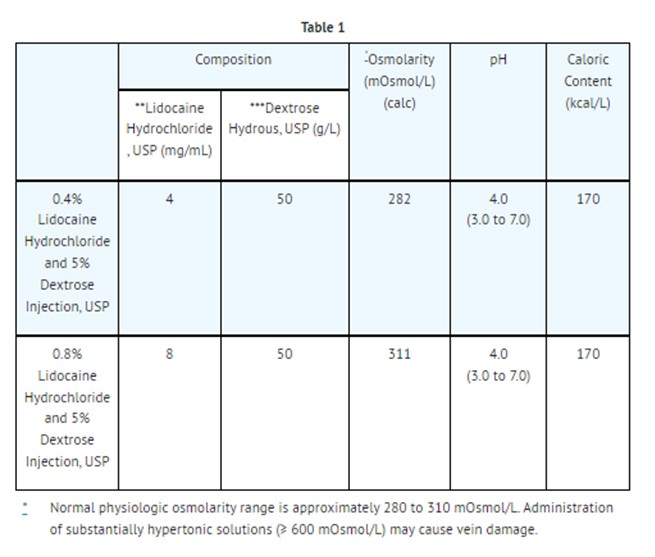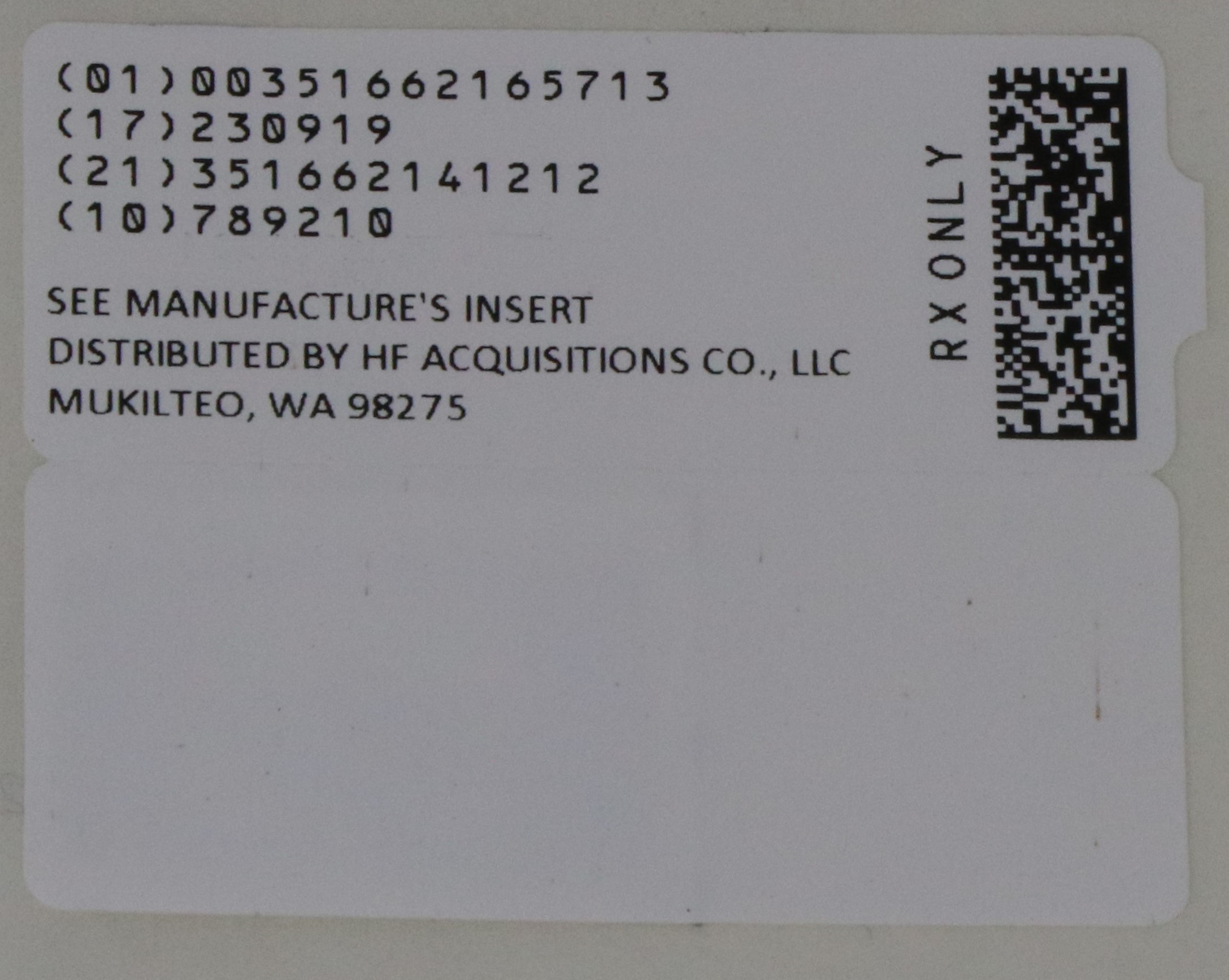 DRUG LABEL: LIDOCAINE HYDROCHLORIDE AND DEXTROSE
NDC: 51662-1657 | Form: INJECTION, SOLUTION
Manufacturer: HF Acquisition Co LLC, DBA HealthFirst
Category: prescription | Type: HUMAN PRESCRIPTION DRUG LABEL
Date: 20240628

ACTIVE INGREDIENTS: LIDOCAINE HYDROCHLORIDE 8 mg/1 mL
INACTIVE INGREDIENTS: SODIUM HYDROXIDE; WATER; DEXTROSE MONOHYDRATE 50 mg/1 mL

DESCRIPTION

Lidocaine Hydrochloride and 5% Dextrose Injection, USP is a sterile, nonpyrogenic solution prepared from lidocaine hydrochloride and dextrose in water for injection. It contains no antimicrobial agents. Lidocaine hydrochloride is designated chemically as 2-(Diethylamino) - 2', 6' - acetoxylidide monohydrochloride. The solution serves as a cardiac antiarrhythmic agent intended for intravenous use. Composition, osmolarity, pH and caloric content are shown in Table 1. The pH is adjusted with sodium hydroxide.

This VIAFLEX Plus plastic container is fabricated from a specially formulated polyvinyl chloride (PL 146 Plastic). VIAFLEX Plus on the container indicates the presence of a drug additive in a drug vehicle. The VIAFLEX Plus plastic container system utilizes the same container as the VIAFLEX plastic container system. The amount of water that can permeate from inside the container into the overwrap is insufficient to affect the solution significantly. Solutions in contact with the plastic container can leach out certain of its chemical components in very small amounts within the expiration period, e.g., di-2-ethylhexyl phthalate (DEHP), up to 5 parts per million. However, the safety of the plastic has been confirmed in tests in animals according to USP biological standards for plastic containers as well as by tissue culture toxicity studies.

CLINICAL PHARMACOLOGY

Mechanism of Action

Lidocaine hydrochloride exerts an antiarrhythmic effect by increasing the electrical stimulation threshold of the ventricle during diastole. In usual therapeutic doses, lidocaine hydrochloride produces no change in myocardial contractility, in systemic arterial pressure, or in absolute refractory period.

Central nervous system adverse reactions become apparent with increasing venous plasma levels above 6.0 μg free base per mL.

Pharmacokinetics

The plasma protein binding of lidocaine is dependent on drug concentration, and the fraction bound decreases with increasing concentration. At concentrations of 1 to 4 micrograms of free base per milliliter 60 to 80 percent of lidocaine is protein bound. Binding is also dependent on the plasma concentration of alpha-1-acid glycoprotein.

Lidocaine crosses the blood-brain and placental barriers, presumably by passive diffusion.

Approximately 90% of lidocaine administered is excreted in the form of various metabolites, and less than 10% is excreted unchanged. Biotransformation includes oxidative N-dealkylation, ring hydroxylation, cleavage of the amide linkage, and conjugation. CYP1A2 and CYP3A4 mediated N-dealkylation, a major pathway of biotransformation, yields the metabolites monoethyl glycine xylidide (MEGX) and glycine xylidide (GX). The pharmacological/toxicological actions of these metabolites are similar to, but less potent than, those of lidocaine. The primary metabolite in urine is a conjugate of 4-hydroxy-2,6-dimethylaniline. The elimination half-life of lidocaine following an intravenous bolus injection is typically 1.5 to 2.0 hours.

Specific Populations

Hepatic Impairment

Because of the rapid rate at which lidocaine is metabolized, any condition that affects liver function may alter lidocaine kinetics. The half-life may be prolonged two-fold or more in patients with liver dysfunction.

Renal Impairment

Mild or moderate renal impairment does not affect lidocaine kinetics; while in patients with severe renal dysfunction, lidocaine clearance is decreased by half and the accumulation of GX increased 1.5-fold.

Lidocaine toxicity is related to systemic blood levels. The decreased clearance and longer half-life of lidocaine should be taken into consideration with prolonged (24 hour) infusions. Constant rate of infusion may result in toxic accumulation of lidocaine.

INDICATIONS AND USAGE

Lidocaine hydrochloride administered intravenously is specifically indicated in the acute management of (1) ventricular arrhythmias occurring during cardiac manipulations, such as cardiac surgery and (2) life-threatening arrhythmias which are ventricular in origin, such as occur during acute myocardial infarction.

CONTRAINDICATIONS

Hypersensitivity reactions, including anaphylactic reactions, have been reported with lidocaine. Lidocaine hydrochloride is contraindicated in patients with a history of hypersensitivity to local anesthetics of the amide type.

Lidocaine is contraindicated in patients with Stokes-Adams syndrome, Wolff-Parkinson-White syndrome, or with severe degrees of sinoatrial, atrioventricular, or intraventricular block.

WARNINGS

Constant monitoring with an electrocardiograph is essential to the administration of lidocaine hydrochloride intravenously. Signs of excessive depression of cardiac conductivity, such as prolongation of the PR interval, widening of the QRS interval and the appearance or aggravation of arrhythmias, should be followed by prompt cessation of the intravenous infusion of this agent. It is mandatory to have emergency resuscitative equipment and drugs immediately available to manage adverse reactions involving cardiovascular, respiratory, or central nervous systems. Central nervous system adverse reactions are associated with venous plasma levels above 6.0 μg free base per mL (see ADVERSE REACTIONS).

Hypersensitivity, including anaphylaxis, has been reported with lidocaine-containing solutions. Stop the infusion immediately if signs of hypersensitivity develop.

Acceleration of ventricular rate may occur in patients with atrial fibrillation or flutter treated with lidocaine.

In patients with sinus bradycardia or incomplete heart block, the administration of lidocaine hydrochloride intravenously for the elimination of ventricular ectopic beats without prior acceleration in heart r ate (e.g., by isoproterenol or by electric pacing) may promote more frequent and serious ventricular arrhythmias or complete heart block (see Contraindications).

Because lidocaine is metabolized mainly in the liver and excreted by the kidneys, patients with renal or hepatic insufficiency may be at increased risk for toxicity.

PRECAUTIONS

General:

If malignant hyperthermia develops, discontinue administration immediately and institute therapeutic countermeasures as clinically indicated.

Lidocaine hydrochloride should not be added to blood transfusion assemblies because of the possibilities of pseudoagglutination or hemolysis.

Laboratory Tests:

Clinical evaluation and periodic laboratory determinations are necessary to monitor changes in fluid balance, electrolyte concentrations, and acid-base balance during prolonged parenteral therapy or whenever the condition of the patient warrants such evaluation.

Drug Interactions:

Pharmacodynamics Interactions

Digitalis derivatives: Monitor toxicity when lidocaine is used in patients with digitalis toxicity accompanied by supraventricular arrhythmia and/or atrioventricular block (see Contraindications).

When lidocaine is administered with other antiarrhythmic drugs such as amiodarone, phenytoin, procainamide, propranolol or quinidine, the cardiac effects may be additive or antagonistic and toxic effects may be additive.

Pharmacokinetics Interactions

Concomitant treatment with drugs which are inhibitors of CYP1A2 and/or CYP3A4 has the potential to increase lidocaine plasma levels by decreasing lidocaine clearance and thereby prolonging the elimination half-life. Monitor toxicity when administering lidocaine with CYP1A2 and/or CYP3A4 inhibitors.

Concomitant use of lidocaineat steady-state concentrations of the CYP1A2 inhibitor fluvoxamine increases intravenous lidocaine plasma AUC and Cmax by 71% and 22%, and decreases MEGX AUC and Cmax by 54% and 65%. Fluvoxamine decreases the plasma clearance of lidocaine by 41%-60% and prolonged the mean half-life by one hour. Monitor toxicity when coadministering these medications.

Concomitant use of lidocaine with propofol, a hypnotic agent and CYP3A4 inhibitor, may increase lidocaine plasma levels by reducing lidocaine clearance. Monitor toxicity when coadministering lidocaine with propofol.

Concomitant treatment with drugs which are inducers of CYP1A2 and/or CYP3A4 (e.g., phenytoin) has the potential to decrease lidocaine plasma levels and higher doses may be required.

Concomitant use of lidocaine with a weak CYP1A2 and CYP3A4 inhibitor has been reported to increase lidocaine plasma levels by 24% – 75% and may result in toxic accumulation of the drug. Monitor toxicity when coadministering lidocaine with cimetidine.

Beta-adrenergic blockers (e.g. propranolol): Concomitant use of lidocaine with beta-adrenergic blockers may increase lidocaine plasma levels by decreasing hepatic blood flow and thereby decrease lidocaine clearance. Monitor for toxicity when coadministering lidocaine with drugs that decrease hepatic blood flow.

Carcinogenesis, Mutagenesis, and Impairment of Fertility:

Long term animal studies have not been performed to evaluate carcinogenic potential, mutagenic potential or the effect on fertility of lidocaine hydrochloride.

Pregnancy:

Teratogenic Effects:

Reproduction studies have been performed in rats at doses up to five times the maximum human dose and have revealed no significant findings. There are, however, no adequate and well-controlled studies in pregnant women. Because animal reproduction studies are not always predictive of human response, physicians should carefully consider the potential risks and benefits for each specific patient before prescribing lidocaine hydrochloride.

Lidocaine may cross the placental barrier.

Nursing Mothers:

Lidocaine is present in human milk. Published studies have reported a range of lidocaine milk: plasma ratios between 0.4-1.1. Limited data available on lidocaine’s effects on the breastfed child have not revealed a consistent pattern of associated adverse events. The development and health benefits of breastfeeding should be considered along with the mother’s clinical need for lidocaine and any potential adverse effects on the breastfed infant from lidocaine or from the underlying maternal condition.

Pediatric Use

Safety and effectiveness in pediatric patients have not been established.

Geriatric Use

Clinical studies of Lidocaine Hydrochloride did not include sufficient numbers of subjects aged 65 and over to determine whether they respond differently from younger subjects. Other reported clinical experience has not identified differences in responses between the elderly and younger patients. In general, dose selection for an elderly patient should be cautious, usually starting at the low end of the dosing range, reflecting the greater frequency of decreased hepatic, renal, or cardiac function, and of concomitant disease or other drug therapy.

ADVERSE REACTIONS

Systemic reactions of the following types have been reported:

Nervous System Disorders: respiratory depression and arrest; unconsciousness; convulsions; tremors; twitching; vomiting; blurred or double vision; drowsiness; dizziness; light-headedness; tinnitus; sensation of heat, cold or numbness; euphoria; apprehension; agitation; confused state; paresthesia; dysarthria.

Cardiovascular System: cardiovascular arrest; bradycardia which may lead to cardiac arrest; hypotension, Ventricular fibrillation, Ventricular tachycardia, Ventricular arrhythmia, Asystole.

Gastrointestinal Disorders: Hypoesthesia oral, Nausea,

Hematologic Effects: methemoglobinemia.

Psychiatric Disorders: Disorientation

Allergic reactions, including anaphylactic reactions, may occur but are infrequent. There have been no reports of cross sensitivity between lidocaine hydrochloride and procainamide or between lidocaine hydrochloride and quinidine.

OVERDOSAGE

Signs and symptoms of overdose may include:

•
Central nervous system effects, e.g., coma, loss of consciousness, CNS depression, seizure, tonic-clonic muscle jerks, tremor, nystagmus, tingling of tongue and lips, tinnitus, drowsiness, disorientation, and lightheadedness.
•
Cardiorespiratory effects, e.g., cardiovascular collapse and cardiorespiratory arrest (sometimes fatal), respiratory depression and arrest, hypotension, myocardial depression, arrhythmias, including asystole, heart block, ventricular arrhythmias, tachycardia, and bradycardia.

Discontinue lidocaine administration in the event of an overdose.

There is no specific antidote for overdose of lidocaine. The risk of overdose can be minimized by close monitoring during treatment.

Emergency procedures should include appropriate corrective, resuscitative, and other supportive measures (See WARNINGS).

DOSAGE AND ADMINISTRATION

Therapy of ventricular arrhythmias is often initiated with a single IV bolus of 1.0 to 1.5 mg/kg at a rate of 25 to 50 mg/min. of lidocaine hydrochloride injection. Following acute treatment by bolus in patients in whom arrhythmias tend to recur and who are incapable of receiving oral antiarrhythmic agents, intravenous infusion of Lidocaine Hydrochloride and 5% Dextrose Injection, USP is administered continuously at the rate of 1 to 4 mg/min (0.020 to 0.050 mg/kg/min in the average 70 kg adult). The 0.4% solution (4 mg/mL) can be given at a rate of 15 to 60 mL/hr (0.25 to 1 mL/min). The 0.8% solution (8 mg/mL) can be given at a rate of 7.5 to 30 mL/hr (0.12 to 0.5 mL/min). Precise dosage regimen is determined by patient characteristics and response.

Infusion rate should be reduced by approximately one-half to compensate for decreased rate of clearance after prolonged infusion (24 hours) (see Clinical Pharmacology). Failure to adjust the rate of infusion in keeping with this altered ability to eliminate lidocaine may result in toxic accumulation of the drug in the patient’s serum.

Intravenous infusions of lidocaine hydrochloride must be administered under constant ECG monitoring to avoid potential overdosage and toxicity. Intravenous infusion should be terminated as soon as the patient’s basic cardiac rhythm appears to be stable or at the earliest signs of toxicity (see OVERDOSAGE). It should rarely be necessary to continue intravenous infusions beyond 24 hours. As soon as possible and when indicated, patients should be changed to an oral antiarrhythmic agent for maintenance therapy.

Caution: When administering lidocaine hydrochloride by continuous infusion, it is advisable to closely monitor the infusion rate. Administer Lidocaine Hydrochloride and 5% Dextrose Injection, USP only with a calibrated infusion device.

Pediatric: Clinical studies to establish pediatric dosing schedules have not been conducted. The usual dosage is a bolus dose of 1 mg/kg followed by an infusion rate of 20 mcg to 50 mcg/kg/min. The bolus dose should be repeated if infusion is not initiated within 15 minutes of the initial bolus dose.

Hepatic impairment is likely to decrease clearance and increase exposure level of lidocaine. Administer lidocaine at lower maintenance infusion rate with close monitoring of toxicity in patients with hepatic impairment.

Renal Impairment: In patients with severe renal impairment (eGFR less than 30 mL/min/1.73 m2), administer lidocaine at lower maintenance infusion rate with close monitoring of toxicity.

Lidocaine is incompatible with the following due to precipitate formation (includes but is not limited to):

•
Amphotericin
•
Cephazolin sodium
•
Phenytoin sodium

Parenteral drug products should be inspected visually for particulate matter and discoloration prior to administration whenever solution and container permit. Do not administer unless solution is clear, the seal is intact, and the container is undamaged. Some opacity of the container plastic due to moisture absorption during the sterilization process may be observed. This is normal and does not affect solution quality or safety. The opacity will diminish gradually. Use of a final filter is recommended during administration of all parenteral solutions, where possible.

Lidocaine must not be infused simultaneously through the same tubing with other medicinal products without first verifying their compatibility.

Set the vent to the close position on a vented intravenous administration set to prevent air embolism.

All injections in VIAFLEX Plus plastic containers are intended for intravenous administration using sterile equipment.

Because dosages of this drug are titrated to response, no additives should be made to Lidocaine Hydrochloride and 5% Dextrose Injection, USP.

HOW SUPPLIED

Lidocaine Hydrochloride and 5% Dextrose Injection, USP in VIAFLEX plastic container is available as follows:

HF Acquisition Co LLC, DBA HealthFirst

11629 49th Pl W,

Mukilteo, WA 98275